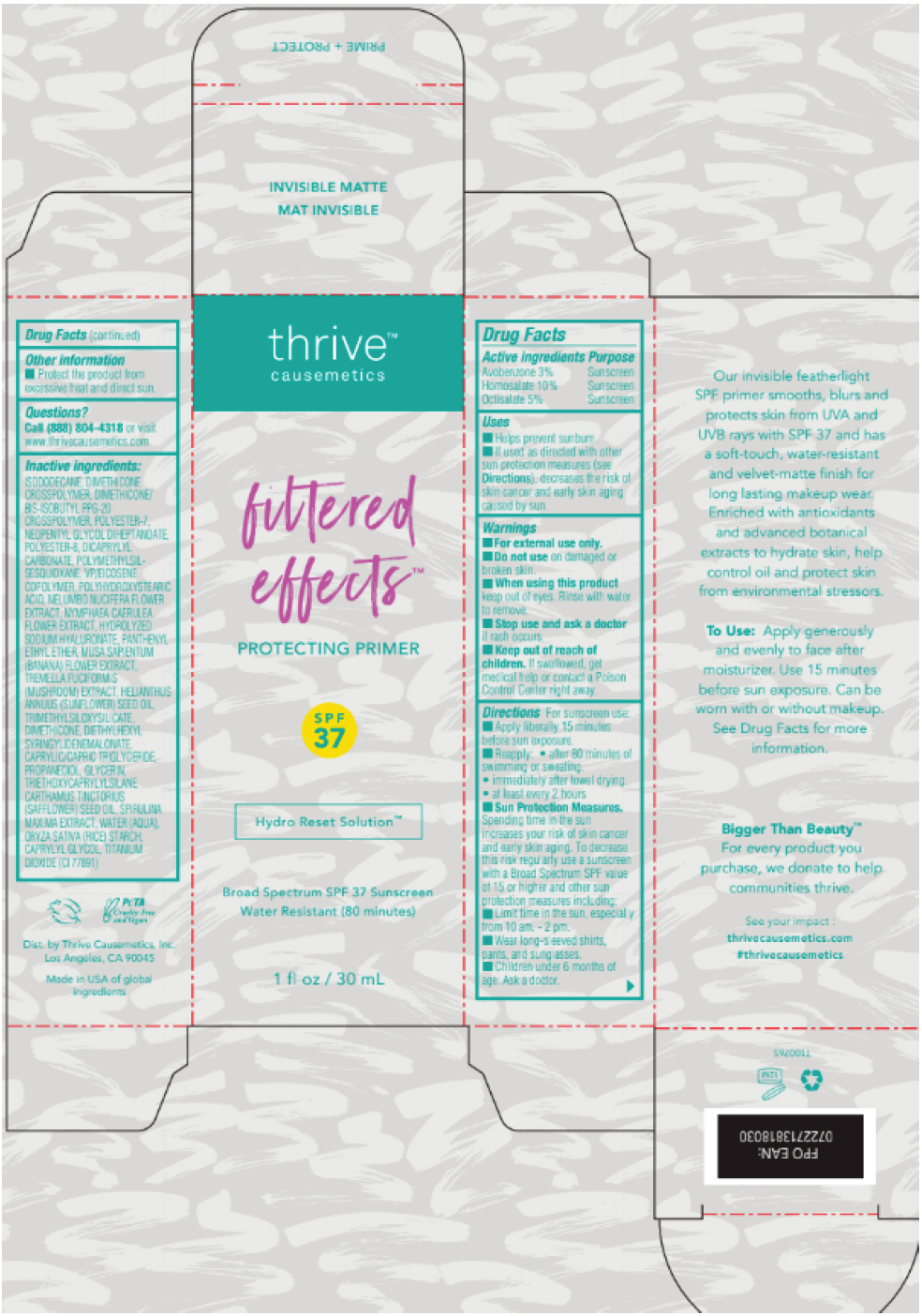 DRUG LABEL: Filtered Effects Protecting Primer Broad Spectrum SPF 37 Sunscreen Water Resistant (80 minutes)
NDC: 77365-006 | Form: GEL
Manufacturer: Thrive Causemetics
Category: otc | Type: HUMAN OTC DRUG LABEL
Date: 20241105

ACTIVE INGREDIENTS: Avobenzone 30 mg/1 mL; Homosalate 100 mg/1 mL; Octisalate 50 mg/1 mL
INACTIVE INGREDIENTS: ISODODECANE; DIMETHICONE CROSSPOLYMER (450000 MPA.S AT 12% IN CYCLOPENTASILOXANE); DIMETHICONE/BIS-ISOBUTYL PPG-20 CROSSPOLYMER; POLYESTER-7; NEOPENTYL GLYCOL DIHEPTANOATE; POLYESTER-8 (1400 MW, CYANODIPHENYLPROPENOYL CAPPED); DICAPRYLYL CARBONATE; POLYMETHYLSILSESQUIOXANE (4.5 MICRONS); EICOSYL POVIDONE; POLYHYDROXYSTEARIC ACID (2300 MW); NELUMBO NUCIFERA FLOWER; NYMPHAEA CAERULEA FLOWER; HYALURONATE SODIUM; PANTHENYL ETHYL ETHER; MUSA X PARADISIACA FLOWER; TREMELLA FUCIFORMIS FRUITING BODY; SUNFLOWER OIL; TRIMETHYLSILOXYSILICATE (M/Q 0.6-0.8); DIMETHICONE; DIETHYLHEXYL SYRINGYLIDENEMALONATE; MEDIUM-CHAIN TRIGLYCERIDES; PROPANEDIOL; GLYCERIN; TRIETHOXYCAPRYLYLSILANE; SAFFLOWER OIL; ARTHROSPIRA MAXIMA; WATER; STARCH, RICE; CAPRYLYL GLYCOL; TITANIUM DIOXIDE

Filtered Effects™ Protecting Primer Broad Spectrum SPF 37 Sunscreen Water Resistant (80 minutes)

Drug Facts

ACTIVE INGREDIENT

Active ingredients | Purpose
Avobenzone 3.0% | Sunscreen
Homosalate 10.0% | Sunscreen
Octisalate 5.0% | Sunscreen

Uses

- Helps prevent sunburn
- If used as directed with other sun protection measures (see Directions), decreases the risk Skin cancer and early skin aging caused by the sun.

Warnings

For external use only

Do not use

- on damaged or broken skin.

When using this product keep out of eyes. Rinse with water to remove.

Stop use and ask a doctor if rash occurs.

Keep out of reach of children. If swallowed, get medical help or contact a Poison Control Center right away.

Directions

For sunscreen use:

- Apply liberally 15 minutes before sun exposure.
- reapply: after 80 minutes of swimming or sweating.
- immediately after towel drying.
- at least every 2 hours.
- Sun Protection Measures: Spending time in the sun increases your risk of skin cancer and early skin aging. To decrease this risk regularly use a sunscreen with a Broad Spectrum SPF value of 15 or higher and other sun protection measures including:
  - Limit time in the sun, especially from 10 am. - 2 pm.
  - Wear long-sleeved shirts, pants, and sunglasses.
- Children under 6 months of age: Ask a doctor.

Other information

- Protect this product from excessive heat and direct sun.

Inactive ingredients

ISODODECANE, DIMETHICONE CROSSPOLYMER, DIMETHICONE/BIS-ISOBUTYL PPG-20 CROSSPOLYMER, POLYESTER-7, NEOPENTYL GLYCOL DIHEPTANOATE, POLYESTER-8, DICAPRYLYL CARBONATE, POLYMETHYLSILSESQUIOXANE, VP/EICOSENE COPOLYMER, POLYHYDROXYSTEARIC ACID, NELUMBO NUCIFERA FLOWER EXTRACT, NYMPHAEA CAERULEA FLOWER EXTRACT, HYDROLYZED SODIUM HYALURONATE, PANTHENYL ETHYL ETHER, MUSA SAPIENTUM (BANANA) FLOWER EXTRACT, TREMELLA FUCIFORMIS (MUSHROOM) EXTRACT, HELIANTHUS ANNUUS (SUNFLOWER) SEED OIL, TRIMETHYLSILOXYSILICATE, DIMETHICONE, DIETHYLHEXYL SYRINGYLIDENEMALONATE, CAPRYLIC/CAPRIC TRIGLYCERIDE, PROPANEDIOL, GLYCERIN, TRIETHOXYCAPRYLYLSILANE, CARTHAMUS TINCTORIUS (SAFFLOWER) SEED OIL, SPIRULINA MAXIMA EXTRACT, WATER (AQUA), ORYZA SATIVA (RICE) STARCH, CAPRYLYL GLYCOL, TITANIUM DIOXIDE (CI 77891)

Questions?

Call (888) 804-4318 or visit www.thrivecausemetics.com

Dist. by Thrive Causemetics, Inc.
Los Angeles, CA 90045

PRINCIPAL DISPLAY PANEL - 30 mL Tube Box

thrive™
causemetics

filtered
effects™

PROTECTING PRIMER

SPF
37

Hydro Reset Solution™

Broad Spectrum SPF 37 Sunscreen
Water Resistant (80 minutes)

1 fl oz / 30 mL